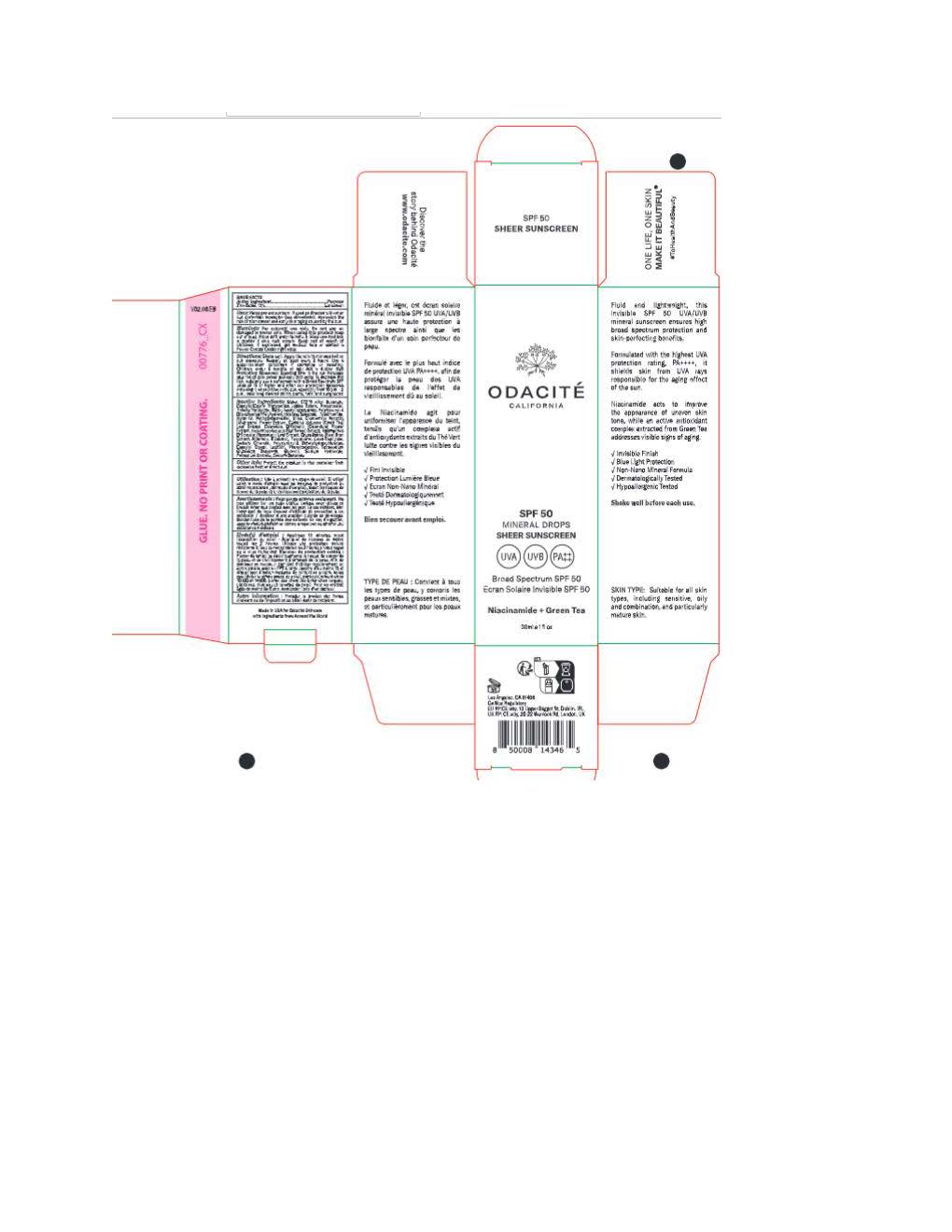 DRUG LABEL: Odacite Mineral Drops Sheer Sunscreen
NDC: 82088-285 | Form: LOTION
Manufacturer: Odacite
Category: otc | Type: HUMAN OTC DRUG LABEL
Date: 20251104

ACTIVE INGREDIENTS: ZINC OXIDE 132 mg/1 mL
INACTIVE INGREDIENTS: ORYZA SATIVA (RICE) BRAN; POLYGLYCERYL-4 DIISOSTEARATE/POLYHYDROXYSTEARATE/SEBACATE; PROPANEDIOL; POLYGLYCERYL-2 DIPOLYHYDROXYSTEARATE; ALKYL (C12-15) BENZOATE; SODIUM CHLORIDE; CAPRYLIC/CAPRIC TRIGLYCERIDE; WATER; COCO-CAPRYLATE; .ALPHA.-BISABOLOL, (+)-; LECITHIN, SOYBEAN; ALLANTOIN; SILICON DIOXIDE; CAPRYLYL GLYCOL; PHENYLPROPANOL; METHYLPROPANEDIOL; GLYCERIN; CAMELLIA SINENSIS LEAF OIL; ROSMARINUS OFFICINALIS FLOWERING TOP OIL; CALENDULA OFFICINALIS SEED OIL; SODIUM HYDROXIDE; NYLON-12; TOCOPHEROL; HYDROLYZED JOJOBA ESTERS (ACID FORM); METHYLHEPTYL ISOSTEARATE; POLYGLYCERYL-3 DIISOSTEARATE; HELIANTHUS ANNUUS (SUNFLOWER) SEED OIL; SODIUM BENZOATE; TETRASODIUM GLUTAMATE DIACETATE; STEARALKONIUM HECTORITE; POTASSIUM SORBATE; TRIDECYL SALICYLATE; NIACINAMIDE

Odacite Mineral Drops Sheer Sunscreen